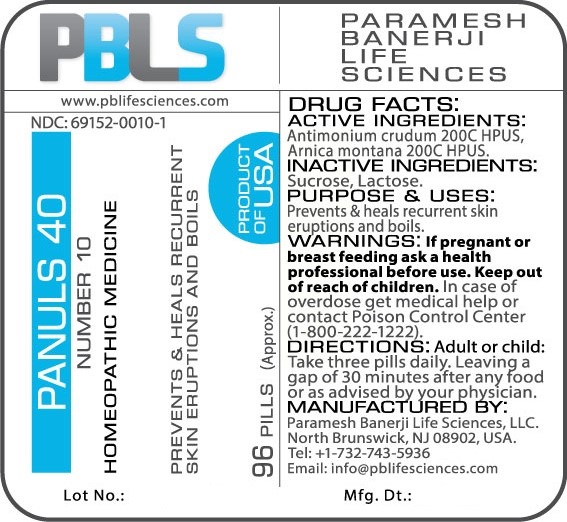 DRUG LABEL: Panuls 40 (Number 10)
NDC: 69152-0010 | Form: PELLET
Manufacturer: Paramesh Banerji Life Sciences LLC
Category: homeopathic | Type: HUMAN OTC DRUG LABEL
Date: 20170717

ACTIVE INGREDIENTS: ANTIMONY TRISULFIDE 200 [hp_C]/1 1; ARNICA MONTANA 200 [hp_C]/1 1
INACTIVE INGREDIENTS: LACTOSE; SUCROSE

DRUG FACTS: Active Ingredients

Antimonium crudum 200C HPUS, Arnica montana 200C HPUS

Inactive Ingredients

Sucrose, Lactose

Purpose

Prevents recurrent skin eruptions and boils

Uses

Prevents recurrent skin eruptions and boils

Warnings

If pregnant or breast feeding ask a health professional before use.

Keep out of reach of children. In case of overdose, get medical help or contact a Poison Control Center (1-800-222-1222) right away.

Direction

Adult or child: Take three pills daily. Leaving a gap of 30 minutes after any food or as advised by your physician.

Manufactured by

Paramesh Banerji Life Sciences, LLC.

North Brunswick, NJ 08902, USA.

Tel: +1-732-743-5936

Email: info@pblifesciences.com

Principal Display Panel

Homeopathic Product

Panuls 40

Number 10

Homeopathic Product

Antimonium crudum 200C HPUS, Arnica montana 200C HPUS

Prevents recurrent skin eruptions and boils

Quantity

96 Pills